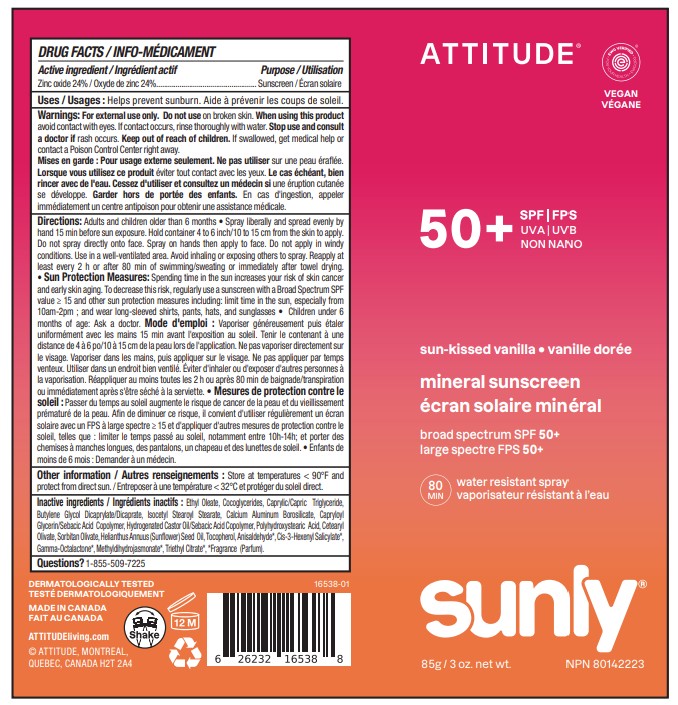 DRUG LABEL: ATTITUDE Sunly Mineral sunscreen Sprayer SPF 50 Sun kissed vanilla
NDC: 61649-538 | Form: SPRAY
Manufacturer: 9055-7588 Québec Inc.DBA ATTITUDE
Category: otc | Type: HUMAN OTC DRUG LABEL
Date: 20251128

ACTIVE INGREDIENTS: ZINC OXIDE 24 g/100 g
INACTIVE INGREDIENTS: METHYLDIHYDROJASMONATE; 3-HEXENYL SALICYLATE, CIS-; ISOCETYL STEAROYL STEARATE; TRIETHYL CITRATE; ANISALDEHYDE; .GAMMA.-OCTALACTONE; ETHYL OLEATE; CAPRYLOYL GLYCERIN/SEBACIC ACID COPOLYMER (2000 MPA.S); CETEARYL OLIVATE; SORBITAN OLIVATE; HYDROGENATED CASTOR OIL/SEBACIC ACID COPOLYMER; COCOGLYCERIDES; BUTYLENE GLYCOL DICAPRYLATE/DICAPRATE; CALCIUM ALUMINUM BOROSILICATE; POLYHYDROXYSTEARIC ACID (2300 MW); CAPRYLIC/CAPRIC TRIGLYCERIDE; TOCOPHEROL; HELIANTHUS ANNUUS (SUNFLOWER) SEED OIL

ATTITUDE Sunly Mineral sunscreen Spray SPF 50 Sun kissed vanilla

DRUG FACTS

ACTIVE INGREDIENT

Zinc oxide (24 %)

PURPOSE

Sunscreen

INDICATIONS AND USAGE

Helps prevent sunburn

WARNINGS

For external use only.

Do not use on broken skin.

When using this product avoid contact with eyes. If contact occurs, rinse thoroughly with water.

Keep out of reach of children. If swallowed, get medical help or contact a Poison Control Center right away.

Stop use and consult a doctor if rash occurs

DOSAGE AND ADMINISTRATION

Adultds and children older than 6 months • Spray liberally and spread evenly by hand 15 min before sun exposure. Hold container 4 to 6 inch/10 to 15 cm from the skin to apply. Do not spray directly onto face. Spray on hands then apply to face. Do not apply in windy conditions. Use in a well-ventilated area. Avoid inhaling or exposing others to spray. Reapply at least every 2 h or after 80 min of swimming/sweating or immediately after towel drying. • Sun Protection Measures: Spending time in the sun increases your risk of skin cancer and early skin aging. To decrease this risk, regularly use a sunscreen with a Broad Spectrum SPF value ≥ 15 and other sun protection measures including: limit time in the sun, especially from 10am-2pm; and wear long-sleeved shirts, pants, hats, and sunglasses • Children under 6 months of age: Ask a doctor.

INACTIVE INGREDIENT

Ethyl Oleate, Cocoglycerides, Caprylic/Capric Triglyceride, Butylene Glycol Dicaprylate/Dicaprate, Isocetyl Stearoyl Stearate, Calcium Aluminum Borosilicate, Capryloyl Glycerin/Sebacic Acid Copolymer, Hydrogenated Castor Oil/Sebacic Acid Copolymer, Polyhydroxystearic Acid, Cetearyl Olivate, Sorbitan Olivate, Helianthus Annuus (Sunflower) Seed Oil, Tocopherol, Methyldihydrojasmonate*, Pentadecalactone*, Phenethyl Acetate*, Triethyl Citrate*, Vanillin*, *Fragrance (Parfum).

STORAGE AND HANDLING

Store at temperatures < 90F and protect from direct sun.

Questions ? 1-855-509-7225

PACKAGE LABEL

ATTITUDE

EWG Verified

VEGAN

SPF 50+

UVA ¦ UVB

NON NANO

sun kissed vanilla

mineral sunscreen

Broad spectrum SPF 50+

80min water resistant spray

sunly

85g / 3 oz. net wt.

NPN 80142223

Made in Canada

Dermatologically tested

Shake